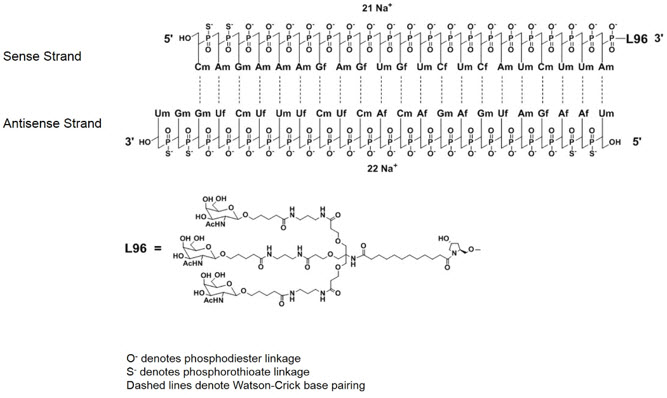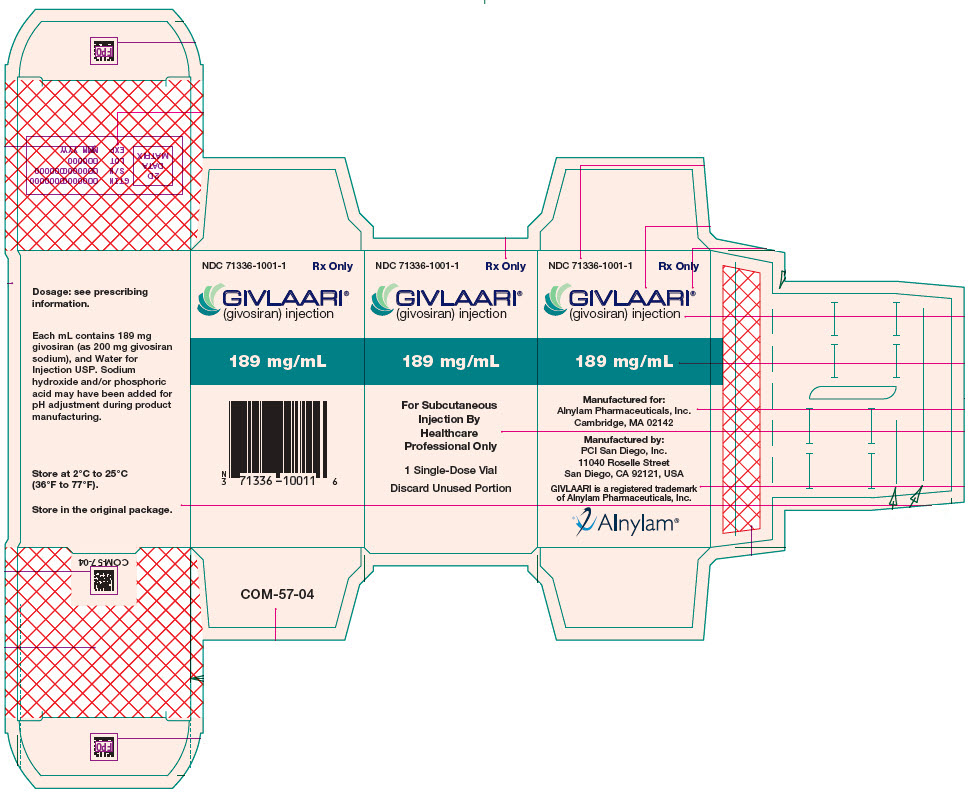 DRUG LABEL: GIVLAARI
NDC: 71336-1001 | Form: INJECTION, SOLUTION
Manufacturer: Alnylam Pharmaceuticals, Inc.
Category: prescription | Type: HUMAN PRESCRIPTION DRUG LABEL
Date: 20250910

ACTIVE INGREDIENTS: givosiran sodium 189 mg/1 mL
INACTIVE INGREDIENTS: WATER

HIGHLIGHTS OF PRESCRIBING INFORMATION

These highlights do not include all the information needed to use GIVLAARI® safely and effectively. See full prescribing information for GIVLAARI.
GIVLAARI (givosiran) injection, for subcutaneous use
Initial U.S. Approval: 2019

1 INDICATIONS AND USAGE

GIVLAARI is an aminolevulinate synthase 1-directed small interfering RNA indicated for the treatment of adults with acute hepatic porphyria (AHP). (1)

2 DOSAGE AND ADMINISTRATION

The recommended dose of GIVLAARI is 2.5 mg/kg once monthly by subcutaneous injection. (2.1)

3 DOSAGE FORMS AND STRENGTHS

Injection: 189 mg/mL in a single-dose vial. (3)

4 CONTRAINDICATIONS

Severe hypersensitivity to givosiran. (4)

5 WARNINGS AND PRECAUTIONS

- Anaphylactic Reaction: Ensure that medical support is available to appropriately manage anaphylactic reactions when administering GIVLAARI. Monitor for signs and symptoms. If anaphylaxis occurs, discontinue GIVLAARI and administer appropriate medical treatment. (5.1)
- Hepatic Toxicity: Measure liver function at baseline and periodically during treatment with GIVLAARI. Interrupt or discontinue treatment with GIVLAARI for severe or clinically significant transaminase elevations. (2.1, 5.2)
- Renal Toxicity: Monitor renal function during treatment with GIVLAARI as clinically indicated. (5.3)
- Injection Site Reactions: May occur, including recall reactions. Monitor for reactions and manage clinically as needed. (5.4)
- Blood Homocysteine Increased: Measure blood homocysteine at baseline and monitor for changes during treatment with GIVLAARI. In patients with elevated blood homocysteine, consider supplementation with vitamin B6 (as monotherapy or multivitamin). (5.5)
- Pancreatitis: Consider acute pancreatitis as a potential diagnosis in GIVLAARI-treated patients with acute upper abdominal pain, clinically significant elevation of pancreatic enzymes and/or imaging findings of acute pancreatitis, to ensure appropriate management. (5.6)

6 ADVERSE REACTIONS

The most common adverse reactions (≥20% of patients) included nausea and injection site reactions. (6.1)

To report SUSPECTED ADVERSE REACTIONS, contact Alnylam Pharmaceuticals at 1-877-256-9526 or FDA at 1-800-FDA-1088 or www.fda.gov/medwatch.

7 DRUG INTERACTIONS

Sensitive CYP1A2 and CYP2D6 Substrates: Avoid concomitant use with CYP1A2 and CYP2D6 substrates for which minimal concentration changes may lead to serious or life-threatening toxicities. (7.1)

FULL PRESCRIBING INFORMATION

1 INDICATIONS AND USAGE

GIVLAARI is indicated for the treatment of adults with acute hepatic porphyria (AHP).

2 DOSAGE AND ADMINISTRATION

2.1 Recommended Dosage

The recommended dose of GIVLAARI is 2.5 mg/kg administered via subcutaneous injection once monthly. Dosing is based on actual body weight.

Missed Dose

Administer GIVLAARI as soon as possible after a missed dose. Resume dosing at monthly intervals following administration of the missed dose.

Dose Modification for Adverse Reactions

In patients with severe or clinically significant transaminase elevations, who have dose interruption and subsequent improvement, reduce the dose to 1.25 mg/kg once monthly [see Warnings and Precautions (5.2)]. In patients who resume dosing at 1.25 mg/kg once monthly without recurrence of severe or clinically significant transaminase elevations, the dose may be increased to the recommended dose of 2.5 mg/kg once monthly.

2.2 Administration Instructions

Ensure that medical support is available to appropriately manage anaphylactic reactions when administering GIVLAARI [see Warnings and Precautions (5.1)].

GIVLAARI is intended for subcutaneous use by a healthcare professional only.

Parenteral drug products should be inspected visually for particulate matter and discoloration prior to administration, whenever solution and container permit. GIVLAARI is a sterile, preservative-free, clear, colorless-to-yellow solution. It is supplied in a single-dose vial, as a ready-to-use solution that does not require additional reconstitution or dilution prior to administration.

Use aseptic technique.

- Calculate the required volume of GIVLAARI based on the recommended weight-based dosage [see Dosage and Administration (2.1)].
- Withdraw the indicated injection volume of GIVLAARI using a 21-gauge or larger needle.
  - Divide doses requiring volumes greater than 1.5 mL equally into multiple syringes.
- Replace the 21-gauge or larger needle with either a 25-gauge or 27-gauge needle with 1/2" or 5/8" needle length.
- Avoid having GIVLAARI on the needle tip until the needle is in the subcutaneous space.
- Administer injection into the abdomen, the back or side of the upper arms, or the thighs. Rotate injection sites. An injection should never be given into scar tissue or areas that are reddened, inflamed, or swollen.
  - If injecting into the abdomen, avoid a 5 cm diameter circle around the navel.
  - If more than one injection is needed for a single dose of GIVLAARI, the injection sites should be at least 2 cm apart from previous injection locations.
- Discard unused portion of the drug.

3 DOSAGE FORMS AND STRENGTHS

Injection: 189 mg/mL clear, colorless-to-yellow solution in a single-dose vial

4 CONTRAINDICATIONS

GIVLAARI is contraindicated in patients with known severe hypersensitivity to givosiran. Reactions have included anaphylaxis [see Warnings and Precautions (5.1)].

5 WARNINGS AND PRECAUTIONS

5.1 Anaphylactic Reaction

Anaphylaxis has occurred with GIVLAARI treatment (<1% of patients in clinical trials) [see Adverse Reactions (6.1)]. Ensure that medical support is available to appropriately manage anaphylactic reactions when administering GIVLAARI. Monitor for signs and symptoms of anaphylaxis. If anaphylaxis occurs, immediately discontinue administration of GIVLAARI and institute appropriate medical treatment.

5.2 Hepatic Toxicity

Transaminase elevations (ALT) of at least 3 times the upper limit of normal (ULN) were observed in 15% of patients treated with GIVLAARI in the placebo-controlled trial [see Adverse Reactions (6.1)]. Transaminase elevations primarily occurred between 3 to 5 months following initiation of treatment.

Measure liver function tests prior to initiating treatment with GIVLAARI, repeat every month during the first 6 months of treatment, and as clinically indicated thereafter. Interrupt or discontinue treatment with GIVLAARI for severe or clinically significant transaminase elevations. For resumption of dosing after interruption, see Dosage and Administration (2.1).

5.3 Renal Toxicity

Increases in serum creatinine levels and decreases in estimated glomerular filtration rate (eGFR) have been reported during treatment with GIVLAARI [see Adverse Reactions (6.1)]. In the placebo-controlled study, 15% of the patients in the GIVLAARI arm experienced a renally-related adverse reaction. The median increase in creatinine at Month 3 was 0.07 mg/dL. Monitor renal function during treatment with GIVLAARI as clinically indicated.

5.4 Injection Site Reactions

Injection site reactions have been reported in 25% of patients receiving GIVLAARI in the placebo-controlled trial. Symptoms included erythema, pain, pruritus, rash, discoloration, or swelling around the injection site. Among 12 patients with reactions, the highest severity of the reaction was mild among 11 (92%) patients and moderate in one (8%) patient. One (2%) patient experienced a single, transient, recall reaction of erythema at a prior injection site with a subsequent dose administration [see Adverse Reactions (6.1)].

5.5 Blood Homocysteine Increased

Increases in blood homocysteine levels have occurred in patients receiving GIVLAARI [see Adverse Reactions (6.1)]. In the ENVISION study, during the open label extension, adverse reactions of blood homocysteine increased were reported in 15 of 93 (16%) patients treated with GIVLAARI. The clinical relevance of the elevations in blood homocysteine during treatment with GIVLAARI is unknown. Measure blood homocysteine levels prior to initiating treatment and monitor for changes during treatment with GIVLAARI. In patients with elevated blood homocysteine levels, assess folate, vitamins B12 and B6. Consider treatment with a supplement containing vitamin B6 (as monotherapy or a multivitamin preparation).

5.6 Pancreatitis

Cases of acute pancreatitis, some severe, have been reported in GIVLAARI-treated patients.

Consider acute pancreatitis as a potential diagnosis in GIVLAARI-treated patients with signs/symptoms of acute pancreatitis including acute upper abdominal pain, clinically significant elevation of pancreatic enzymes, and/or imaging findings of acute pancreatitis, to ensure appropriate management. Consider interruption and/or discontinuation of GIVLAARI treatment for severe cases.

6 ADVERSE REACTIONS

The following clinically significant adverse reactions are discussed in greater detail in other sections of the labeling:

- Anaphylactic Reaction [see Warnings and Precautions (5.1)]
- Transaminase Elevations [see Warnings and Precautions (5.2)]
- Serum Creatinine Increase [see Warnings and Precautions (5.3)]
- Injection Site Reactions [see Warnings and Precautions (5.4)]
- Blood Homocysteine Increased [see Warnings and Precautions (5.5)]
- Pancreatitis [see Warnings and Precautions (5.6)]

6.1 Clinical Trial Experience

Because clinical trials are conducted under widely varying conditions, adverse reaction rates observed in the clinical trials of a drug cannot be directly compared to rates in the clinical trials of another drug and may not reflect the rates observed in practice.

In the pivotal placebo-controlled, double-blind study (ENVISION), 48 patients received 2.5 mg/kg GIVLAARI and 46 patients received placebo, administered once monthly via subcutaneous injection for up to 6 months. Patients received GIVLAARI for a median of 5.5 months (range 2.7-6.4 months). Of these, 47 patients received ≥5 months of treatment. The most frequently occurring (≥20% incidence) adverse reactions reported in patients treated with GIVLAARI were nausea (27%) and injection site reactions (25%). Permanent discontinuation occurred in one patient due to elevated transaminases.

Table 1: Adverse Reactions that Occurred at Least 5% More Frequently in Patients Treated with GIVLAARI Compared to Patients Treated with Placebo
Adverse Reaction | GIVLAARI N=48 N (%) | Placebo N=46 N (%)
Nausea | 13 (27) | 5 (11)
Injection site reactions | 12 (25) | 0
Rash [Grouped term includes pruritus, eczema, erythema, rash, rash pruritic, urticaria] | 8 (17) | 2 (4)
Serum creatinine increase [Grouped term includes blood creatinine increased, glomerular filtration rate decreased, chronic kidney disease (decreased eGFR)] | 7 (15) | 2 (4)
Transaminase elevations | 6 (13) | 1 (2)
Fatigue | 5 (10) | 2 (4)

Adverse reactions observed at a lower frequency occurring in placebo-controlled and open-label clinical studies included anaphylactic reaction (one patient, 0.9%) and hypersensitivity (one patient, 0.9%).

In the ENVISION study, during the open label extension, adverse reactions of blood homocysteine increased were reported in 15 of 93 (16%) patients treated with GIVLAARI [see Warnings and Precautions (5.5)].

6.2 Immunogenicity

As with all oligonucleotides, there is a potential for immunogenicity. The detection of antibody formation is highly dependent on the sensitivity and specificity of the assay. Additionally, the observed incidence of antibody (including neutralizing antibody) positivity in an assay may be influenced by several factors, including assay methodology, sample handling, timing of sample collection, concomitant medications, and underlying disease. For these reasons, comparison of the incidence of antibodies in the studies described below with the incidence of antibodies in other studies or to other products may be misleading.

In placebo-controlled and open-label clinical studies, 1 of 111 patients with AHP (0.9%) developed treatment-emergent anti-drug antibodies (ADA) during treatment with GIVLAARI. No clinically significant differences in the clinical efficacy, safety, pharmacokinetic, or pharmacodynamic profiles of GIVLAARI were observed in the patient who tested positive for anti-givosiran antibodies.

6.3 Postmarketing Experience

The following additional adverse reactions have been reported during post-approval use. Because these events are reported voluntarily from a population of uncertain size, it is generally not possible to reliably estimate their frequency or establish a causal relationship to drug exposure.

Gastrointestinal Disorders: Acute pancreatitis

7 DRUG INTERACTIONS

7.1 Effect of GIVLAARI on Other Drugs

Sensitive CYP1A2 and CYP2D6 Substrates

Concomitant use of GIVLAARI increases the concentration of CYP1A2 or CYP2D6 substrates [see Clinical Pharmacology (12.3)], which may increase adverse reactions of these substrates. Avoid concomitant use of GIVLAARI with CYP1A2 or CYP2D6 substrates, for which minimal concentration changes may lead to serious or life-threatening toxicities. If concomitant use is unavoidable, decrease the CYP1A2 or CYP2D6 substrate dosage in accordance with approved product labeling.

8 USE IN SPECIFIC POPULATIONS

8.1 Pregnancy

Risk Summary

In animal reproduction studies, subcutaneous administration of givosiran to pregnant rabbits during the period of organogenesis resulted in adverse developmental outcomes at doses that produced maternal toxicity (see Data).

There are no available data with GIVLAARI use in pregnant women to evaluate a drug-associated risk of major birth defects, miscarriage, or adverse maternal or fetal outcomes. Consider the benefits and risks of GIVLAARI for the mother and potential adverse effects to the fetus when prescribing GIVLAARI to a pregnant woman.

The estimated background risk of major birth defects and miscarriage in the indicated population is unknown. All pregnancies have a background risk of birth defect, loss, or other adverse outcomes. In the U.S. general population, the estimated background risk of major birth defects and miscarriage in clinically recognized pregnancies is 2% to 4% and 15% to 20%, respectively.

Clinical Considerations

Disease-associated maternal and/or embryo/fetal risk

Porphyria attacks during pregnancy, often triggered by hormonal changes, occur in 24% to 95% of AHP patients, with maternal mortality ranging from 2% to 42%. Pregnancy in AHP patients is associated with higher rates of spontaneous abortion, hypertension and low birth weight infants.

Data

Animal Data

In an embryo-fetal development study in pregnant rabbits, givosiran was administered subcutaneously at doses of 0.5, 1.5, and 5 mg/kg/day during organogenesis (gestational days 7-19) or 20 mg/kg as a single administration on gestation day 7. Administration of givosiran was maternally toxic based on decreased body weight gain at all dose levels tested and resulted in increased postimplantation loss starting at 1.5 mg/kg/day. An increased incidence of skeletal variations of the sternebrae was observed at 20 mg/kg. The 1.5 mg/kg/day dose in rabbits is 5 times the maximum recommended human dose (MRHD) of 2.5 mg/kg/month normalized to 0.089 mg/kg/day, based on body surface area. In a combined fertility and embryo-fetal development study in female rats, givosiran was administered subcutaneously at doses of 0.5 to 5 mg/kg/day during organogenesis (gestational days 6-17). The 5 mg/kg/day dose (9 times the normalized MRHD based on body surface area) was associated with a skeletal variation (incomplete ossification of pubes) and produced maternal toxicity.

In a pre- and postnatal development study, givosiran administered subcutaneously to pregnant rats on gestation days 7, 13, and 19 and postnatal days 6, 12, and 18 at doses up to 30 mg/kg did not produce maternal toxicity or developmental effects in the offspring.

8.2 Lactation

Risk Summary

There are no data on the presence of GIVLAARI in human milk, the effects on the breastfed child, or the effects on milk production. The developmental and health benefits of breastfeeding should be considered along with the mother's clinical need for GIVLAARI and any potential adverse effects on the breastfed child from GIVLAARI or from the underlying maternal condition.

8.4 Pediatric Use

Safety and effectiveness in pediatric patients have not been established.

8.5 Geriatric Use

Clinical studies of GIVLAARI did not include sufficient numbers of patients aged 65 and over to determine whether they respond differently from younger patients.

11 DESCRIPTION

GIVLAARI is an aminolevulinate synthase 1-directed small interfering RNA (siRNA), covalently linked to a ligand containing three N-acetylgalactosamine (GalNAc) residues to enable delivery of the siRNA to hepatocytes.

The structural formulas of the givosiran drug substance in its sodium form, and the ligand (L96), are presented below.

Abbreviations: Af = adenine 2'-F ribonucleoside; Cf = cytosine 2'-F ribonucleoside; Uf = uracil 2'-F ribonucleoside; Am = adenine 2'-OMe ribonucleoside; Cm = cytosine 2'-OMe ribonucleoside; Gf = guanine 2'-F ribonucleoside; Gm = guanine 2'-OMe ribonucleoside; Um = uracil 2'-OMe ribonucleoside; L96 = triantennary GalNAc (N-acetylgalactosamine)

GIVLAARI is supplied as a sterile, preservative-free, 1-mL colorless-to-yellow solution for subcutaneous injection containing 189 mg givosiran in a single-dose, 2-mL Type 1 glass vial with a fluoropolymer-coated rubber stopper and a flip-off aluminum seal. GIVLAARI is available in cartons containing one single-dose vial each. GIVLAARI is formulated in Water for Injection. Sodium hydroxide and/or phosphoric acid may have been added for pH adjustment during product manufacturing.

The molecular formula of givosiran sodium is C524 H651 F16 N173 Na43 O316 P43 S6 with a molecular weight of 17,245.56 Da.

The molecular formula of givosiran (free acid) is C524 H694 F16 N173 O316 P43 S6 with a molecular weight of 16,300.34 Da.

12 CLINICAL PHARMACOLOGY

12.1 Mechanism of Action

Givosiran is a double-stranded small interfering RNA that causes degradation of aminolevulinate synthase 1 (ALAS1) mRNA in hepatocytes through RNA interference, reducing the elevated levels of liver ALAS1 mRNA. This leads to reduced circulating levels of neurotoxic intermediates aminolevulinic acid (ALA) and porphobilinogen (PBG), factors associated with attacks and other disease manifestations of AHP.

12.2 Pharmacodynamics

The pharmacodynamic effects of GIVLAARI were evaluated in chronic high excreters treated with 0.035 to 2.5 mg/kg single dose and AHP patients treated with 2.5 to 5 mg/kg once monthly and 2.5 to 5 mg/kg once quarterly dose via subcutaneous injection. Dose-dependent reduction in urinary ALAS1 mRNA, ALA and PBG levels was observed over the 0.035 to 5 mg/kg dose range (0.14 to 2-fold the approved recommended dosage). Median reductions from baseline in urinary ALA and PBG of 83.7% and 75.1%, respectively, were observed 14 days after the first dose of GIVLAARI 2.5 mg/kg once monthly in AHP patients. Maximal reductions in ALA and PBG levels were achieved around Month 3, with median reductions from baseline of 93.8% for ALA and 94.5% for PBG, and were sustained thereafter with repeated once monthly dosing.

Cardiac Electrophysiology

The effect of GIVLAARI on the QTc interval was evaluated in a double-blind, placebo-controlled study and the open-label extension in 94 patients. No large mean increase in QTc (i.e. >20 ms) was detected at the 2.5 mg/kg once monthly dose level. A dedicated thorough QT study has not been conducted with GIVLAARI.

12.3 Pharmacokinetics

The pharmacokinetics of givosiran and its active metabolite [AS(N-1)3′ givosiran] were evaluated following single and multiple dosing in chronic high excreter subjects and AHP patients as summarized in Table 2.

Table 2. Pharmacokinetic Parameters of Givosiran and Its Active Metabolite
 |  | Givosiran | AS(N-1)3′ Givosiran
General Information
Steady-State Exposure | Cmax [Mean (CV%)] | 321 ng/mL (51%) | 123 ng/mL (64%)
Steady-State Exposure | AUC24 [Mean (CV%)] | 4130 ng∙h/mL (43%) | 1930 ng∙h/mL (63%)
Dose Proportionality |  | - Steady-state maximum plasma concentration (Cmax) and area under the curve (AUC) for givosiran and AS(N-1)3′ givosiran increase proportionally over the 0.35 mg/kg to 2.5 mg/kg once monthly dose range (0.14 to 1-fold the approved recommended dosage). - Cmax and AUC for givosiran and AS(N-1)3′ givosiran increase slightly greater than proportionally at doses greater than 2.5 mg/kg once monthly.
Accumulation |  | - No accumulation of givosiran or AS(N-1)3′ givosiran was observed following multiple dosing.
Absorption
Tmax [Median (range)] |  | 3 (0.5-8) hours | 7 (1.5-12) hours
Distribution
Apparent Central Volume of Distribution (Vz/F) [Mean (RSE%)] [Based on population PK model estimation.] |  | 10.4 L (2.3%)
Protein Binding |  | 90% [Givosiran plasma protein binding was concentration-dependent and decreased with increasing givosiran concentrations (from 92% at 1 µg/mL to 21% at 50 µg/mL).] | Not evaluated
Organ Distribution |  | Givosiran and AS(N-1)3′ givosiran distribute primarily to the liver after subcutaneous dosing.
Elimination
Half-Life [Mean (CV%)] |  | 6 hours (46%) | 6 hours (41%)
Apparent Clearance [Mean (CV%)] |  | 35.1 L/hr (18%) | 64.7 L/hr (33%)
Metabolism
Primary Pathway |  | Givosiran is metabolized by nucleases to oligonucleotides of shorter lengths. Givosiran is not a substrate of CYP enzymes [Based on in vitro study result.] .
Active Metabolite |  | The active metabolite, AS(N-1)3′ givosiran, is equipotent to givosiran in plasma and the AUC0-24 represents 45% of givosiran AUC, at the approved recommended givosiran dosage.
Excretion
Primary Pathway |  | The dose recovered in urine was 5%-14% as givosiran and 4%-13% as AS(N-1)3′ givosiran [After single and multiple subcutaneous doses of givosiran 2.5 mg/kg and 5 mg/kg.] .

Specific Populations

No clinically meaningful differences in givosiran pharmacokinetics or pharmacodynamics (percent reduction in urinary ALA and PBG) were observed based on age (19 to 65 years), sex, race/ethnicity, mild, moderate or severe renal impairment (eGFR ≥15 to <89 mL/min/1.73m^2 estimated by the Modification of Diet in Renal Disease [MDRD] formula), and mild hepatic impairment (bilirubin ≤1×ULN and AST >1×ULN, or bilirubin >1×ULN to 1.5×ULN).The effect of end-stage renal disease (eGFR <15 mL/min/1.73m^2), and moderate to severe hepatic impairment on givosiran pharmacokinetics is unknown.

Drug Interaction Studies

Clinical Studies

Effect of givosiran on CYP1A2 Substrates: Concomitant use of a single subcutaneous dose of givosiran 2.5 mg/kg increased caffeine (sensitive CYP1A2 substrate) AUC by 3.1-fold and Cmax by 1.3-fold [see Drug Interactions (7.1)].

Effect of givosiran on CYP2D6 Substrates: Concomitant use of a single subcutaneous dose of givosiran 2.5 mg/kg increased dextromethorphan (sensitive CYP2D6 substrate) AUC by 2.4-fold and Cmax by 2.0-fold [see Drug Interactions (7.1)].

Effect of givosiran on other CYP450 Substrates: Concomitant use of a single subcutaneous dose of givosiran 2.5 mg/kg increased losartan (CYP2C9 substrate) AUC by 1.1-fold with no change in Cmax; increased omeprazole (sensitive CYP2C19 substrate) AUC by 1.6-fold and Cmax by 1.1-fold; increased midazolam (sensitive CYP3A4 substrate) AUC by 1.5-fold and Cmax by 1.2-fold. These changes in exposure were not considered clinically relevant.

In Vitro Studies

Effect of givosiran on CYP450 Enzymes: In vitro studies indicate that givosiran does not directly inhibit or induce CYP enzymes; however, because of its pharmacological effects on the hepatic heme biosynthesis pathway, givosiran has the potential to reduce the activity of CYP enzymes in the liver.

13 NONCLINICAL TOXICOLOGY

13.1 Carcinogenesis, Mutagenesis, Impairment of Fertility

In a carcinogenicity study in Sprague Dawley rats administered 25, 50, or 100 mg/kg givosiran by subcutaneous injection every 28 days for up to 89 weeks (males) or 85 weeks (females), givosiran doses in rats were 2, 3, and 6 times, respectively, the MRHD based on body surface area. A statistically significant increase in hepatocellular adenomas occurred in males at 100 mg/kg/month, the clinical significance of which is uncertain.

In a carcinogenicity study in male and female Tg.rasH2 mice administered givosiran by subcutaneous injection every 28 days for 26 weeks, up to 1500 mg/kg, givosiran was not carcinogenic.

Givosiran was not genotoxic in the in vitro bacterial reverse mutation (Ames) assays, an in vitro chromosomal aberration assay in cultured human peripheral blood lymphocytes or the in vivo micronucleus assay in rats.

In fertility and early embryonic development studies, givosiran administered subcutaneously once weekly at doses up to 30 mg/kg in male and female rats prior to and during mating, and continuing in females throughout organogenesis, resulted in no adverse effects on fertility or reproductive function in male or female animals.

14 CLINICAL STUDIES

The efficacy of GIVLAARI in patients with acute hepatic porphyria was evaluated in the ENVISION trial (NCT03338816), a randomized, double-blind, placebo-controlled, multinational study.

ENVISION enrolled 94 patients with acute hepatic porphyria (AHP) (89 patients with AIP, 2 patients with variegate porphyria [VP], 1 patient with hereditary coproporphyria [HCP], and 2 patients with no identified mutation). Eligible patients were randomized 1:1 to receive once monthly subcutaneous injections of GIVLAARI 2.5 mg/kg or placebo during the 6-month double-blind period. In this study, inclusion criteria specified a minimum of 2 porphyria attacks requiring hospitalization, urgent healthcare visit, or intravenous hemin administration at home in the 6 months prior to study entry. After the 6 month treatment period patients were enrolled in an open label extension period for up to 30 months. Ninety-three patients were enrolled in the open label extension period. Hemin use during the study was permitted for the treatment of acute porphyria attacks.

The median age of patients studied was 37.5 years (range 19 to 65 years), 89% of patients were female, and 78% were white. GIVLAARI and placebo arms were balanced with respect to historical porphyria attack rate, hemin prophylaxis prior to study entry, use of opioid medications, and patient-reported measures of pain symptoms between attacks.

Efficacy in the 6-month double-blind period was measured by the rate of porphyria attacks that required hospitalizations, urgent healthcare visit, or intravenous hemin administration at home.

Efficacy results for GIVLAARI are provided in Table 3. On average, AHP patients on GIVLAARI experienced 70% (95% CI: 60%, 80%) fewer porphyria attacks compared to placebo.

Table 3. Rate of Porphyria Attacks [Attacks that require hospitalization, urgent healthcare visits, or intravenous hemin administration at home.] and Days of Hemin Use in Patients with AHP Over the 6-Month Double-blind Period of ENVISION
 | Patients with AHP
 | GIVLAARI (N=48) | Placebo (N=46)
Mean Rate (95% CI) of Porphyria Attacks | 1.9 (1.3, 2.8) | 6.5 (4.5, 9.3)
Rate Ratio [Adjusted for prior hemin prophylaxis status and historical attack rates. A ratio <1 represents a favorable outcome for GIVLAARI.] (95% CI) (GIVLAARI/placebo) | 0.3 [p < 0.0001] (0.2, 0.4)
Mean Days (95% CI) of Hemin Use | 4.7 (2.8, 7.9) | 12.8 (7.6, 21.4)
Ratio (95% CI) (GIVLAARI/placebo) | 0.3 [p = 0.0002] (0.1, 0.5)

GIVLAARI also resulted in a reduction in hemin use, urinary ALA, and urinary PBG.

16 HOW SUPPLIED/STORAGE AND HANDLING

16.1 How Supplied

GIVLAARI (givosiran) is a clear, colorless-to-yellow ready-to-use solution available in single-dose vials of 189 mg/mL in cartons containing one vial (NDC 71336-1001-1).

16.2 Storage and Handling

Store at 2°C to 25°C (36°F to 77°F).

Store GIVLAARI in its original container until ready for use.

17 PATIENT COUNSELING INFORMATION

Advise patients of the potential risks of GIVLAARI treatment:

- Anaphylactic Reaction: Inform patients about the risk and possible symptoms of severe hypersensitivity reactions that could occur [see Warnings and Precautions (5.1)].
- Hepatic Toxicity: Inform patients that transaminase elevations may occur, and that laboratory testing will be conducted in the first 6 months of treatment and as clinically indicated thereafter [see Warnings and Precautions (5.2)].
- Renal Toxicity: Inform patients that increases in serum creatinine and decreases in eGFR have been reported and that laboratory testing will be conducted as clinically indicated [see Warnings and Precautions (5.3)].
- Injection Site Reactions: Inform patients of the signs and symptoms of injection site reactions (examples include redness, pain, itching, rash, discoloration, or localized swelling) [see Warnings and Precautions (5.4)].
- Blood Homocysteine Increased: Inform patients that increases in blood homocysteine levels have been reported when using GIVLAARI, and that laboratory testing will be conducted prior to and during treatment with GIVLAARI. Vitamin supplementation may be considered for elevated blood homocysteine levels [see Warnings and Precautions (5.5)].

Manufactured for: Alnylam Pharmaceuticals, Inc., Cambridge, MA 02142
Manufactured by: PCI San Diego, Inc., 11049 Roselle Street, San Diego, CA 92121

GIVLAARI is a registered trademark of Alnylam Pharmaceuticals, Inc.

PRINCIPAL DISPLAY PANEL - 189 mg/mL Vial Carton

NDC 71336-1001-1
Rx Only

GIVLAARI®
(givosiran) injection

189 mg/mL

For Subcutaneous
Injection By
Healthcare
Professional Only

1 Single-Dose Vial

Discard Unused Portion